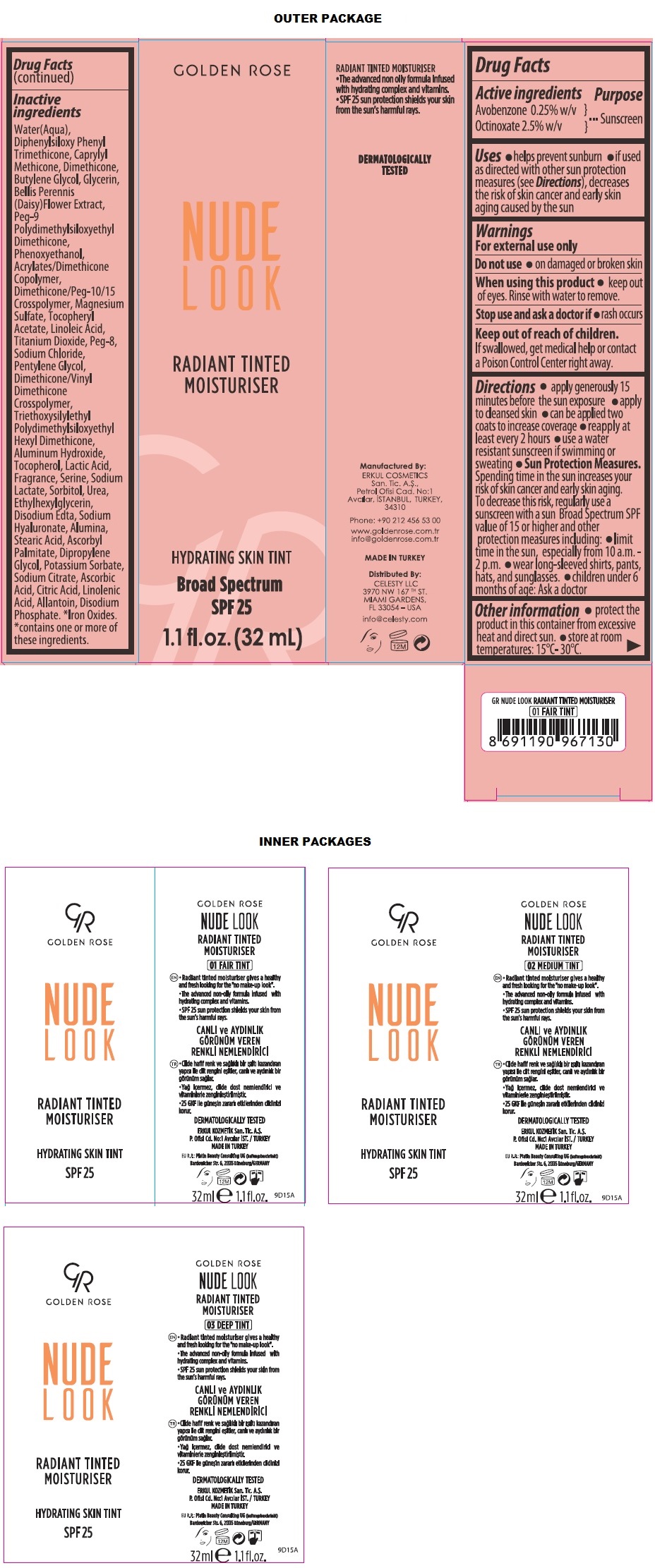 DRUG LABEL: GR NUDE LOOK SPF 25
NDC: 82715-103 | Form: CREAM
Manufacturer: ERKUL KOZMETIK SANAYI VE TICARET ANONIM SIRKETI
Category: otc | Type: HUMAN OTC DRUG LABEL
Date: 20250806

ACTIVE INGREDIENTS: AVOBENZONE 0.25 g/100 mL; OCTINOXATE 2.5 g/100 mL
INACTIVE INGREDIENTS: WATER; DIPHENYLSILOXY PHENYL TRIMETHICONE; CAPRYLYL TRISILOXANE; DIMETHICONE, UNSPECIFIED; BUTYLENE GLYCOL; GLYCERIN; BELLIS PERENNIS FLOWER; PEG-9 POLYDIMETHYLSILOXYETHYL DIMETHICONE; PHENOXYETHANOL; 2-ETHYLHEXYL ACRYLATE, METHACRYLATE, METHYL METHACRYLATE, OR BUTYL METHACRYLATE/HYDROXYPROPYL DIMETHICONE COPOLYMER (30000-300000 MW); DIMETHICONE/PEG-10/15 CROSSPOLYMER; MAGNESIUM SULFATE, UNSPECIFIED FORM; .ALPHA.-TOCOPHEROL ACETATE; LINOLEIC ACID; TITANIUM DIOXIDE; POLYETHYLENE GLYCOL 400; SODIUM CHLORIDE; PENTYLENE GLYCOL; DIMETHICONE/VINYL DIMETHICONE CROSSPOLYMER (SOFT PARTICLE); TRIETHOXYSILYLETHYL POLYDIMETHYLSILOXYETHYL HEXYL DIMETHICONE; ALUMINUM HYDROXIDE; TOCOPHEROL; LACTIC ACID, UNSPECIFIED FORM; SERINE; SODIUM LACTATE; SORBITOL; UREA; ETHYLHEXYLGLYCERIN; EDETATE DISODIUM ANHYDROUS; HYALURONATE SODIUM; ALUMINUM OXIDE; STEARIC ACID; ASCORBYL PALMITATE; DIPROPYLENE GLYCOL; POTASSIUM SORBATE; SODIUM CITRATE, UNSPECIFIED FORM; ASCORBIC ACID; CITRIC ACID MONOHYDRATE; LINOLENIC ACID; ALLANTOIN; SODIUM PHOSPHATE, DIBASIC, ANHYDROUS; FERRIC OXIDE RED; FERRIC OXIDE YELLOW; FERROSOFERRIC OXIDE

GR GOLDEN ROSE NUDE LOOK RADIANT TINTED MOISTURISER

Active ingredients

Avobenzone 0.25% w/v
Octinoxate 2.5% w/v

Purpose

Sunscreen

Uses

• helps prevent sunburn • if used as directed with other sun protection measures (see Directions), decreases the risk of skin cancer and early skin aging caused by the sun

Warnings

For external use only

Do not use • on damaged or broken skin

When using this product • keep out of eyes. Rinse with water to remove.

Stop use and ask a doctor if • rash occurs

Keep out of reach of children.
If swallowed, get medical help or contact a Poison Control Center right away.

Directions

• apply generously 15 minutes before the sun exposure • apply to cleansed skin • can be applied two coats to increase coverage • reapply at least every 2 hours • use a water resistant sunscreen if swimming or sweating
• Sun Protection Measures. Spending time in the sun increases your risk of skin cancer and early skin aging. To decrease this risk, regularly use a sunscreen with a sun Broad Spectrum SPF value of 15 or higher and other protection measures including: • limit time in the sun, especially from 10 a.m. - 2 p.m. • wear long-sleeved shirts, pants, hats, and sunglasses. • children under 6 months of age: Ask a doctor

Other information

• protect the product in this container from excessive heat and direct sun. • store at room temperatures: 15°C- 30°C.

Inactive ingredients

Water(Aqua), Diphenylsiloxy Phenyl Trimethicone, Caprylyl Methicone, Dimethicone, Butylene Glycol, Glycerin, Bellis Perennis (Daisy) Flower Extract, Peg-9 Polydimethylsiloxyethyl Dimethicone, Phenoxyethanol, Acrylates/Dimethicone Copolymer, Dimethicone/Peg-10/15 Crosspolymer, Magnesium Sulfate, Tocopheryl Acetate, Linoleic Acid, Titanium Dioxide, Peg-8, Sodium Chloride, Pentylene Glycol, Dimethicone/Vinyl Dimethicone Crosspolymer, Triethoxysilylethyl Polydimethylsiloxyethyl Hexyl Dimethicone, Aluminum Hydroxide, Tocopherol, Lactic acid, Fragrance, Serine, Sodium Lactate, Sorbitol, Urea, Ethylhexylglycerin, Disodium Edta, Sodium Hyaluronate, Alumina, Stearic Acid, Ascorbyl Palmitate, Dipropylene Glycol, Potassium Sorbate, Sodium Citrate, Ascorbic Acid, Citric Acid, Linolenic Acid, Allantoin, Disodium Phosphate. *Iron Oxides.
*contains one or more of these ingredients.

GOLDEN ROSE

RADIANT TINTED MOISTURISER

HYDRATING SKIN TINT

Broad Spectrum SPF 25

01 FAIR TINT

02 MEDIUM TINT

03 DEEP TINT

• Radiant tinted moisturiser gives a healthy and fresh looking for the "no make-up look".
• The advanced non oily formula infused with hydrating complex and vitamins.
• SPF 25 sun protection shields your skin from the sun's harmful rays.

DERMATOLOGICALLY TESTED

Manufactured By:
ERKUL COSMETICS San. Tic. A.Ş.,
Petrol Ofisi Cad. No:1
Avcılar, ISTANBUL, TURKEY,
34310

Phone: +90 212 456 53 00

www.goldenrose.com.tr
info@goldenrose.com.tr

MADE IN TURKEY

Distributed By:
CELESTY LLC
3970 NW 167TH ST.
MIAMI GARDENS,
FL 33054 – USA

info@celesty.com

EU R.P: Platin Beauty Consulting UG
(haftungsbeschränkt)
Bardowicker Str. 6, 21335
Lüneburg/GERMANY